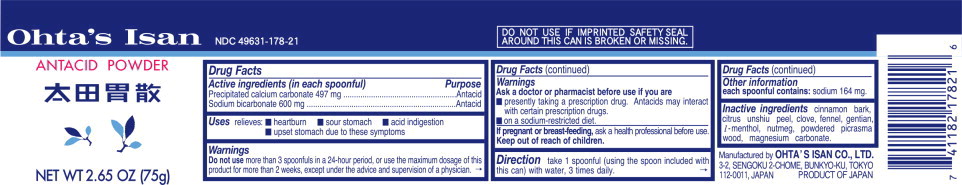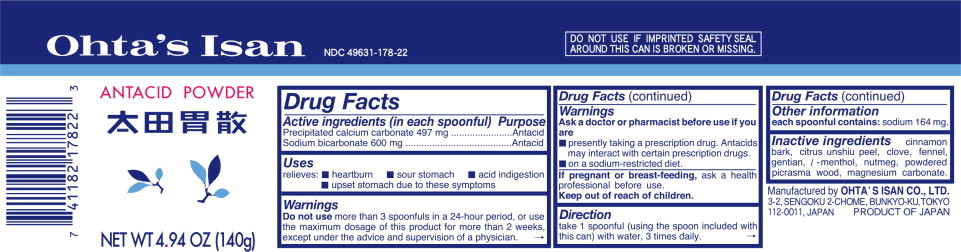 DRUG LABEL: OHTAS ISAN ANTACID
NDC: 49631-178 | Form: POWDER
Manufacturer: OHTA'S ISAN CO.,LTD.
Category: otc | Type: HUMAN OTC DRUG LABEL
Date: 20241021

ACTIVE INGREDIENTS: CALCIUM CARBONATE 1 g/1 g; SODIUM BICARBONATE 1 g/1 g
INACTIVE INGREDIENTS: CINNAMON; TANGERINE; CLOVE; FENNEL; GENTIANA LUTEA ROOT; LEVOMENTHOL; NUTMEG; PICRASMA QUASSIOIDES WOOD; MAGNESIUM CARBONATE

Active Ingredients (in each spoonful)

Precipitated calcium carbonate 497 mg
Sodium bicarbonate 600 mg

Purpose

Precipitated calcium carbonate ............. Antacid
Sodium bicarbonate ............................. Antacid

Uses

relieves: ■ heartburn ■ sour stomach ■ acid indigestion ■ upset stomach due to these symptoms

Warnings

Do not use more than 3 spoonfuls in a 24-hour period, or use the maximum dosage of this product for more than 2 weeks, except under the advice and supervision of a physician.

Ask a doctor or pharmacist before use if you are

■ presently taking a prescription drug. Antacids may interact with certain prescription drugs.
■ on a sodium-restricted diet.

If pregnant or breast-feeding,

ask a health professional before use.

Direction

take 1 spoonful (using the spoon included with this can) with water, 3 times daily.

Other Information

each spoonful contains: sodium 164 mg.

Inactive ingredients

cinnamon bark, citrus unshiu peel, clove, fennel, gentian, l-menthol, nutmeg, powdered picrasma wood, magnesium carbonate.

Principal Display Panel - Can Label

Ohta's Isan NDC 49631-178-21

ANTACID POWDER

NET WT 2.65 OZ (75g)

Principal Display Panel - Can Label

Ohta's Isan NDC 49631-178-22

ANTACID POWDER

NET WT 4.94 OZ (140g)